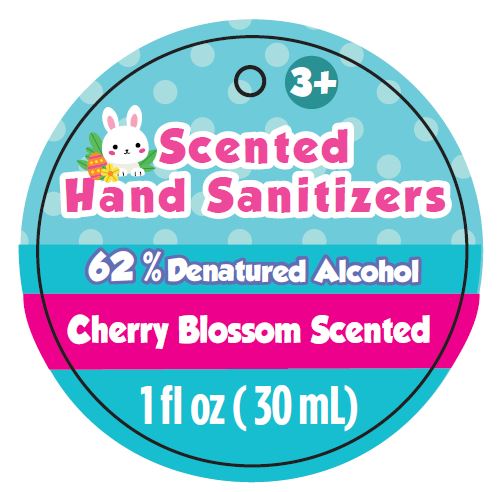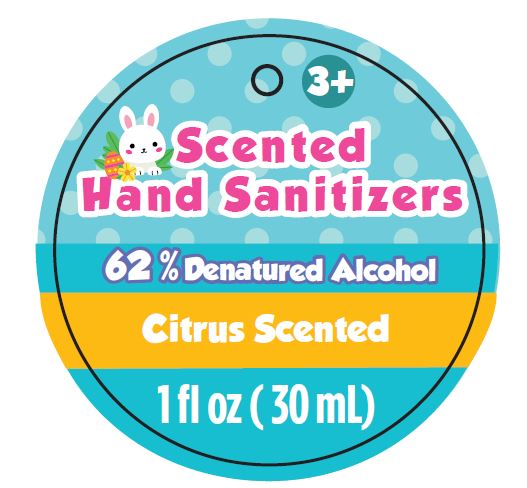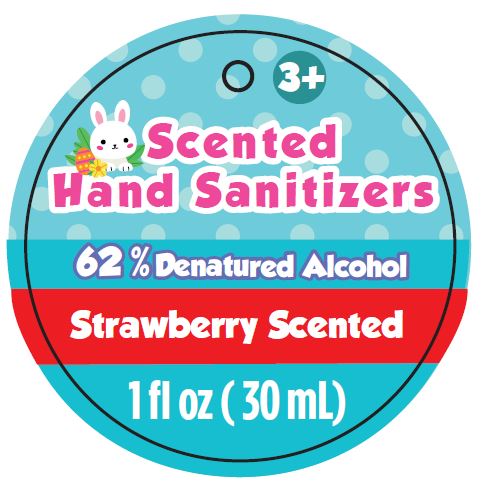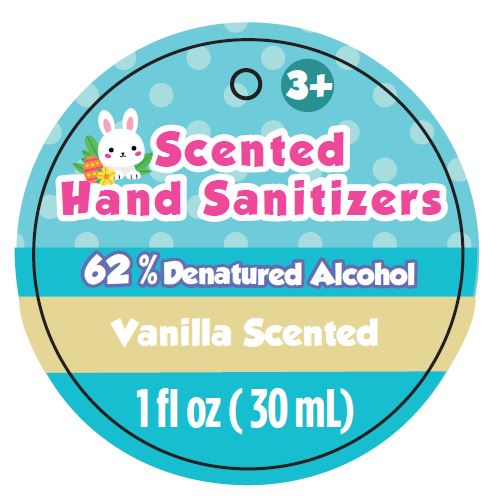 DRUG LABEL: Scented Hand Sanitizer - Citrus Scented
NDC: 80652-001 | Form: GEL
Manufacturer: Little Kids, Inc.
Category: otc | Type: HUMAN OTC DRUG LABEL
Date: 20200916

ACTIVE INGREDIENTS: ALCOHOL 62 mL/100 mL
INACTIVE INGREDIENTS: FD&C YELLOW NO. 5; CARBOMER INTERPOLYMER TYPE A (55000 CPS); GLYCERIN; PROPYLENE GLYCOL; WATER; TROLAMINE; ALOE VERA LEAF; MALTODEXTRIN

Active Ingredient

Denatured Ethyl alcohol 62% v/v.

Purpose

Antiseptic

Uses

- To decrease bacteria on the skin that could cause disease .
- For use when soap and water are not available.

Warnings

For external use only.

Flammable. Keep away from fire or flame.

When using this product:

- keep out of eyes. In case of contact with eyes, flush eyes thoroughly with water.
- on open skin wounds.
- on children less than 2 months of age.

Do Not Use:

- on children less than 2 months of age.
- on open skin wounds

Stop use and ask a doctor if irritation or rash occurs. These may be signs of a serious condition.

Keep out of reach of children. If swallowed, get medical help or contact a Poison Control Center right away.

Directions

- Place enough product on hands to cover all surfaces. Rub hands together until dry.
- Supervise children under 6 years of age when using this product to avoid swallowing.

Other information

- do not store above 105oF

Inactive ingredients

Aloe Barbadensis Leaf Juice, Acrylates/C10-30 Alkyl Acrylate, Crosspolymer, Fragrance, Glycerin, Maltodextrin, Propylene Glycol, Triethanolamine, Water, D&C Red NO.33, FD&C Yellow No.5, FD&C Blue No.1.